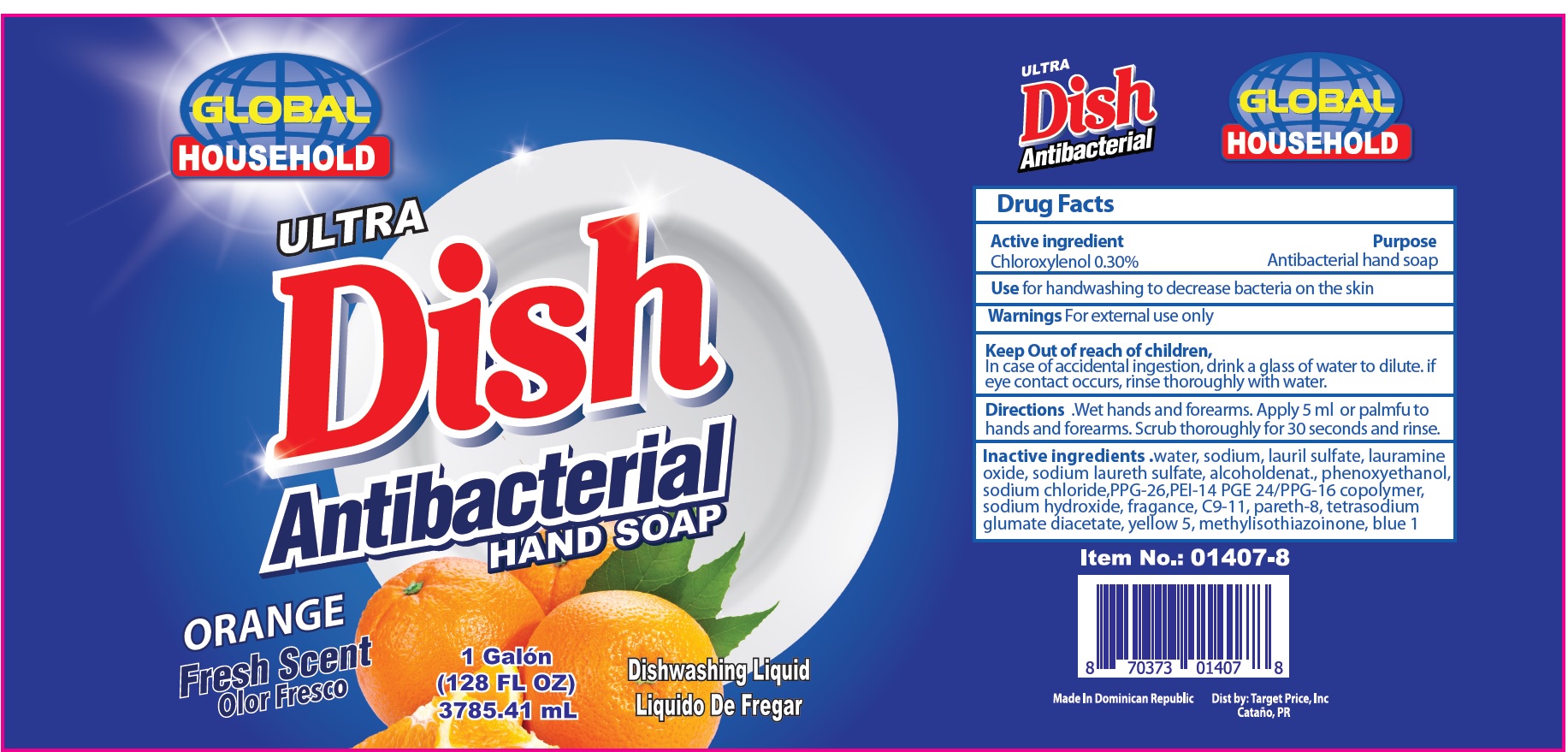 DRUG LABEL: Global Household Antibacterial Hand Orange
NDC: 72146-046 | Form: GEL
Manufacturer: Target Price Inc
Category: otc | Type: HUMAN OTC DRUG LABEL
Date: 20200915

ACTIVE INGREDIENTS: CHLOROXYLENOL 3 mg/1 mL
INACTIVE INGREDIENTS: WATER; SODIUM; LAURYL SULFATE; LAURAMINE OXIDE; SODIUM LAURETH-3 SULFATE; ALCOHOL; PHENOXYETHANOL; SODIUM CHLORIDE; PPG-26; SODIUM HYDROXIDE; TETRASODIUM GLUTAMATE DIACETATE; FD&C YELLOW NO. 5; METHYLISOTHIAZOLINONE; FD&C BLUE NO. 1

Global Household Antibacterial Hand Soap Orange

Active Ingredient

Chloroxylenol 0.30%

Purpose

Antibacterial hand soap

USE

for handwashing to decrease bacteria on the skin

Warnings

For external use only

Keep Out of reach of children,

In case of accidental ingestion, drink a glass of water to dilute. if eye contact occurs, rinse thoroughly with water.

Directions

- Wet hands and forearms. Apply 5 ml or palmfu to hands and forearms. Scrub thoroughly for 30 seconds and rinse.

Inactive ingredients.

- water, sodium, lauril sulfate, lauramine oxide, sodium laureth sulfate, alcoholdenat., phenoxyethanol,sodium chloride,PPG-26,PEI-14 PGE 24/PPG-16 copolymer, sodium hydroxide, fragance, C9-11, pareth-8, tetrasodium glumate diacetate, yellow 5, methylisothiazoinone, blue 1